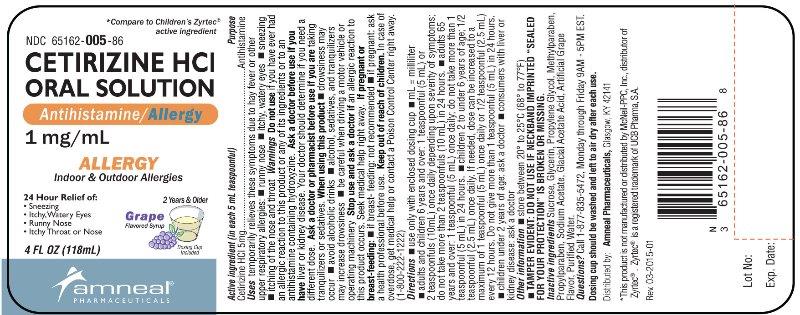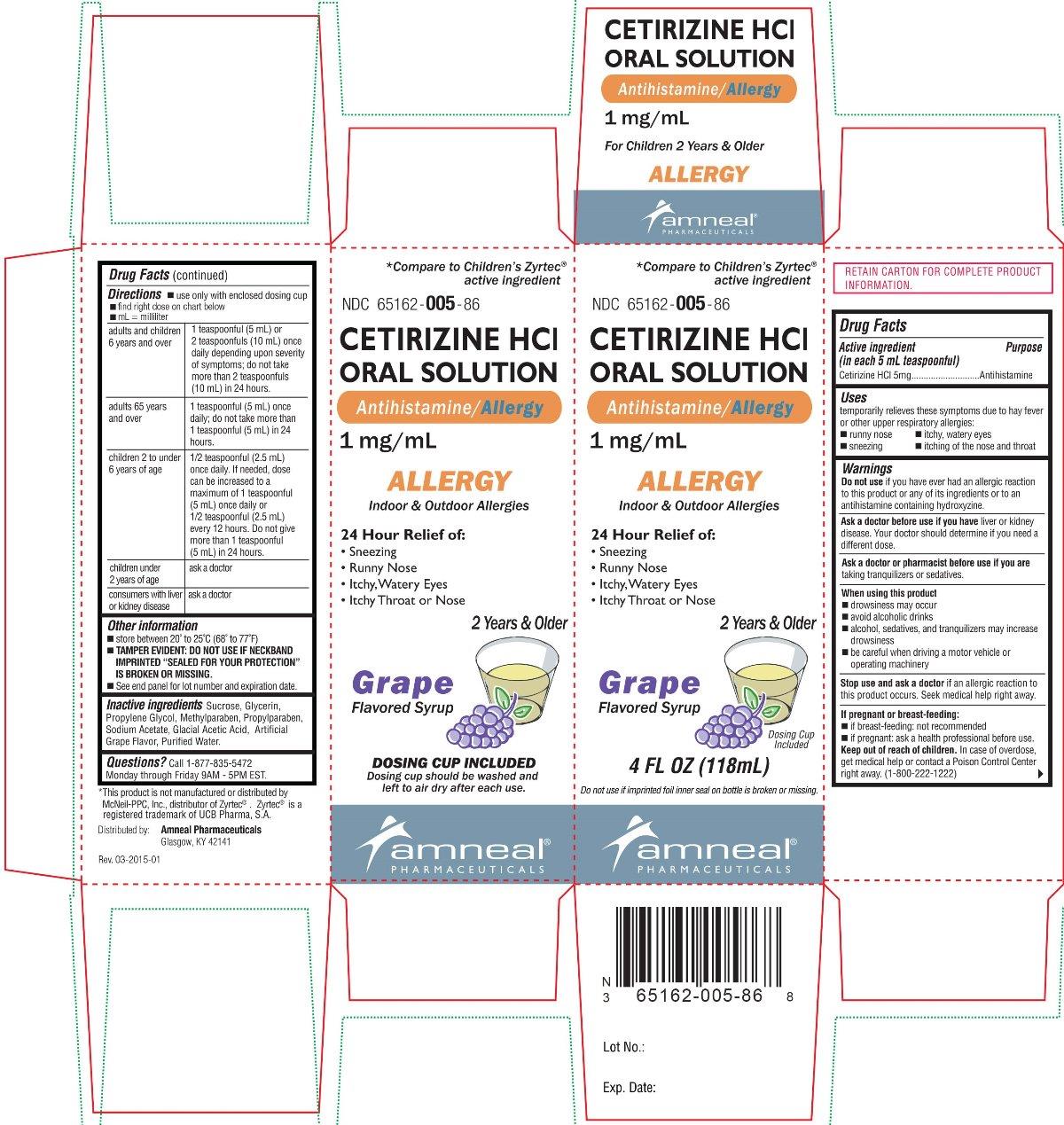 DRUG LABEL: Cetirizine Hydrochloride
NDC: 65162-005 | Form: SOLUTION
Manufacturer: Amneal Pharmaceuticals LLC
Category: otc | Type: HUMAN OTC DRUG LABEL
Date: 20241023

ACTIVE INGREDIENTS: CETIRIZINE HYDROCHLORIDE 5 mg/5 mL
INACTIVE INGREDIENTS: ACETIC ACID; GLYCERIN; METHYLPARABEN; PROPYLENE GLYCOL; PROPYLPARABEN; SODIUM ACETATE; SUCROSE; WATER

Cetirizine Hydrochloride Oral Solution
Antihistamine/ Allergy
1 mg/mL

*Compared to Children’s Zyrtec® active ingredient

Drug Facts

ACTIVE INGREDIENT

(in each 5 mL teaspoonful)

Cetirizine HCl 5 mg

PURPOSE

Antihistamine

Uses

temporarily relieves these symptoms due to hay fever or other upper respiratory allergies:

- runny nose
- sneezing
- itchy, watery eyes
- itching of the nose and throat

WARNINGS

Do not use if you have ever had an allergic reaction to this product or any of its ingredients or to an antihistamine containing hydroxyzine.

Ask a doctor before use if you have liver or kidney disease. Your doctor should determine if you need a different dose.

Ask a doctor or pharmacist before use if you are taking tranquilizers or sedatives.

When using this product

- drowsiness may occur
- avoid alcoholic drinks
- alcohol, sedatives, and tranquilizers may increase drowsiness
- be careful when driving a motor vehicle or operating machinery

Stop use and ask a doctor if an allergic reaction to this product occurs. Seek medical help right away.

If pregnant or breastfeeding:

- if breast-feeding: not recommended
- if pregnant: ask a health professional before use

Keep out of reach of children. In case of overdose, get medical help of contact a Poison Control Center right away. (1-800-222-1222)

Directions

- use only with enclosed dosing cup
- find right dose on chart below
- mL = milliliter

adults and children 6 years and over | 1 teaspoonful (5 mL) or 2 teaspoonfuls (10 mL) once daily depending upon severity of symptoms; do not take more than 2 teaspoonfuls (10 mL) in 24 hours.
adults 65 years and over | 1 teaspoonful (5 mL) once daily; do not take more than 1 teaspoonful (5 mL) in 24 hours.
children 2 to under 6 years of age | ½ teaspoonful (2.5 mL) once daily. If needed, dose can be increased to a maximum of 1 teaspoonful (5 mL) once daily or ½ teaspoonful (2.5 mL) every 12 hours. Do not give more than 1 teaspoonful (5 mL) in 24 hours.
children under 2 years of age | ask a doctor
consumers with liver or kidney disease | ask a doctor

Other information

- store between 20° to 25°C (68° to 77°F)
- TAMPER EVIDENT: DO NOT USE IF NECKBAND IMPRINTED “SEALED FOR YOUR PROTECTION” IS BROKEN OR MISSSING.

INACTIVE INGREDIENTS

Sucrose, Glycerin, Propylene Glycol, Methylparaben, Propylparaben, Sodium Acetate, Glacial Acetic Acid, Artificial Grape Flavor, Purified Water.

Questions?

Call 1-877-835-5472

Monday through Friday 9AM – 5PM EST.

*This product is not manufactured or distributed by McNeil-PPC, Inc., distributor of Zyrtec® . Zyrtec® is a registered trademark of UCB Pharma, S.A.

Distributed by: Amneal Pharmaceuticals
Glasgow, KY 42141

Rev. 03-2015-01